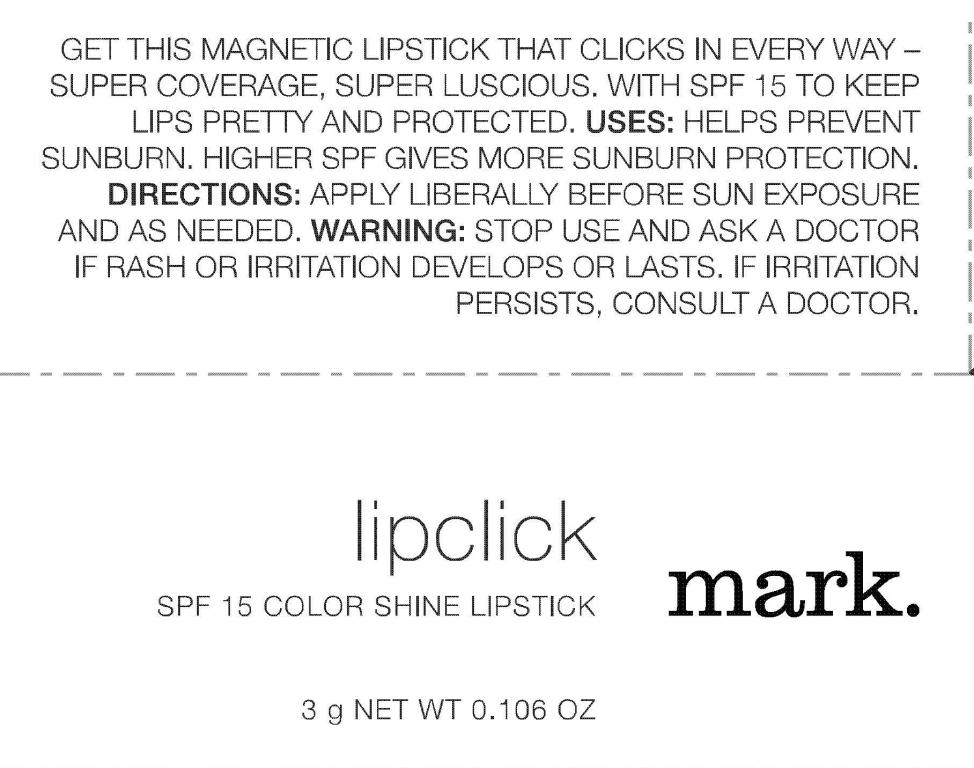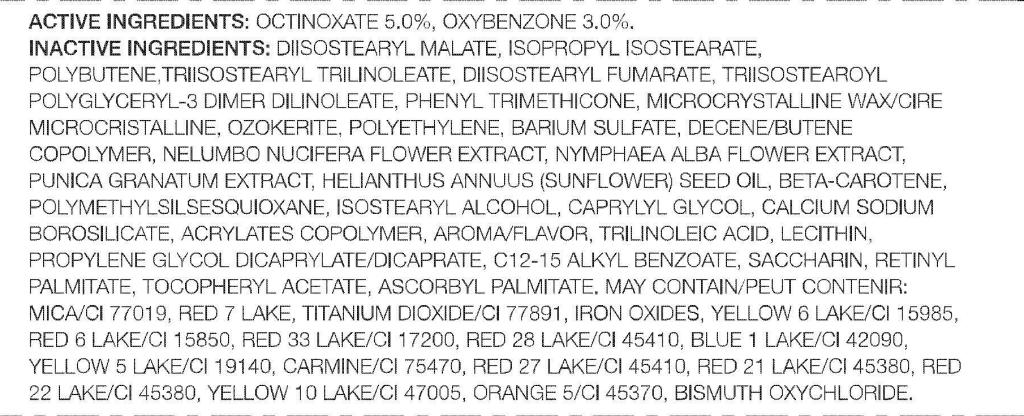 DRUG LABEL: mark. Lipclick
NDC: 10096-0236 | Form: LIPSTICK
Manufacturer: Avon Products, Inc.
Category: otc | Type: HUMAN OTC DRUG LABEL
Date: 20101220

ACTIVE INGREDIENTS: OCTINOXATE	 0.15 g/3 g; OXYBENZONE	 0.09 g/3 g
INACTIVE INGREDIENTS: MICROCRYSTALLINE WAX	; BARIUM SULFATE	; BETA CAROTENE	; CAPRYLYL GLYCOL	; C12-15 ALKYL BENZOATE	; SACCHARIN	; ASCORBYL PALMITATE 	

INDICATIONS AND USAGE

USES: HELPS PREVENT SUNBURN. HIGHER SPF GIVES MORE SUNBURN PROTECTION.

DOSAGE AND ADMINISTRATION

DIRECTIONS: APPLY LIBERALLY BEFORE SUN EXPOSURE AND AS NEEDED.

WARNINGS

WARNING: STOP USE AND ASK A DOCTOR IF RASH OR IRRITATION DEVELOPS OR LASTS. IF IRRITATION PERSISTS, CONSULT A DOCTOR.

ACTIVE INGREDIENTS: OCTINOXATE 5.0% OXYBENZONE 3.0%

INACTIVE INGREDIENTS:

DIISOSTEARYL MALATE
ISOPROPYL ISOSTEARATE
POLYBUTENE
TRIISOSTEARYL TRILINOLEATE
DIISOSTEARYL FUMARATE
TRIISOSTEAROYL POLYGLYCERYL-3 DIMER DILINOLEATE
PHENYL TRIMETHICONE
MICROCRYSTALLINE WAX/CIRE MICROCRISTALLINE
OZOKERITE
POLYETHYLENE
BARIUM SULFATE
DECENE/BUTENE COPOLYMER
NELUMBO NUCIFERA FLOWER EXTRACT
NYMPHAEA ALBA FLOWER EXTRACT
PUNICA GRANATUM EXTRACT
HELIANTHUS ANNUUS (SUNFLOWER) SEED OIL
BETA-CAROTENE
POLYMETHYLSILSESQUIOXANE
ISOSTEARYL ALCOHOL
CAPRYLYL GLYCOL
CALCIUM SODIUM BOROSILICATE
ACRYLATES COPOLYMER
AROMA/FLAVOR
TRILINOLEIC ACID
LECITHIN
PROPYLENE GLYCOL DICAPRYLATE/DICAPRATE
C12-15 ALKYL BENZOATE
SACCHARIN
RETINYL PALMITATE
TOCOPHERYL ACETATE
ASCORBYL PALMITATE
MAY CONTAIN:
MICA/CI 77019
RED 7 LAKE
TITANIUM DIOXIDE/CI 77891
IRON OXIDES
YELLOW 6 LAKE/CI 15985
RED 6 LAKE/CI 15850
RED 33 LAKE/CI 17200
RED 28 LAKE/CI 45410
BLUE 1 LAKE/CI 42090
YELLOW 5 LAKE/CI 19140
CARMINE/CI 75470
RED 27 LAKE/CI 45410
RED 21 LAKE/CI 45380
RED 22 LAKE/CI 45380
YELLOW 10 LAKE/CI 47005
ORANGE 5/CI 45370
BISMUTH OXYCHLORIDE